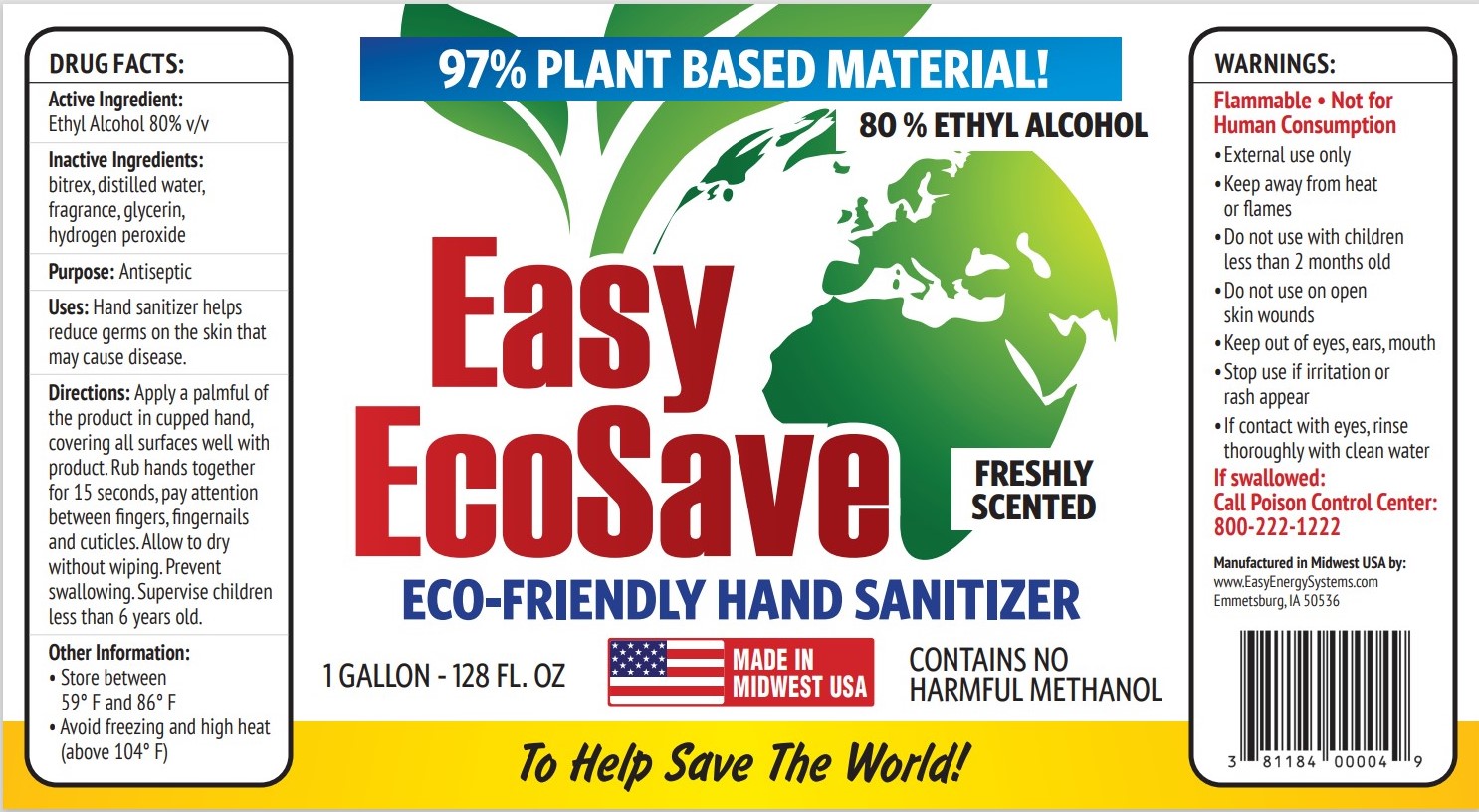 DRUG LABEL: 80% with Denaturant and Fragrance
NDC: 81184-005 | Form: LIQUID
Manufacturer: Easy Energy Systems, Inc.
Category: otc | Type: HUMAN OTC DRUG LABEL
Date: 20210719

ACTIVE INGREDIENTS: ALCOHOL 3028 mL/3785 mL
INACTIVE INGREDIENTS: COUMARIN 17.94 mL/3785 mL; GLYCEROL FORMAL 54.9 mL/3785 mL; HYDROGEN PEROXIDE 4.73 mL/3785 mL; WATER 679 mL/3785 mL; DENATONIUM BENZOATE ANHYDROUS 15.1 mg/3785 mL

This is a hand sanitizer manufactured according to the Temporary Policy for Preparation of Certain Alcohol-Based Hand Sanitizer Products During the Public Health Emergency (CoViD-19); Guidance for Industry.

The hand sanitizer is manufactured using only the following United States Pharmacopoeia (USP) grade ingredients in the preparation of the product (percentage in final product formulation) consistent with World Health Organization (WHO) recommendations:

1. Alcohol (ethanol) (USP or Food Chemical Codex (FCC) grade) (80%, volume/volume (v/v)) in an aqueous solution denatured according to Alcohol and Tobacco Tax and Trade Bureau regulations in 27 CFR part 20.
2. Glycerol (1.45% v/v).
3. Hydrogen peroxide (0.125% v/v).
4. Sterile distilled water or boiled cold water.
5. Denaturant
6. Fragrance

Active Ingredient(s)

Ethyl Alcohol 80% v/v

Purpose

Antiseptic

Uses

Hand Sanitizer helps reduce germs on the skin that may cause disease.

Warnings

Flammable. Not for Human Consumption

• External Use Only

• Keep away from heat or flame

- Do not use with children less than 2 months old
- Do not use on open skin wounds

WHEN USING

If contact with eyes, rinse thoroughly with clean water.

Stop use if irritation or rash appear.

KEEP OUT OF REACH OF CHILDREN

If swallowed, Call Poison Control Center: 800 - 222 - 1222

Directions

Apply a palmful of the product in cupped hand, covering all surfaces well with product.

Rub hands together for 15 seconds, pay attention between fingers, fingernails and cuticles.

Allow to dry without wiping.

Prevent swallowing.

Supervise children less than 6 years old.

Other information

- Store between 59° F and 86° F
- Avoid freezing and high heat (above 104° F)

Inactive ingredients

bitrex, distilled water, fragrance, glycerin, hydrogen peroxide

RECENT MAJOR CHANGES

We are adding a different product (81184-005-05), so this is the new label for that new product.

It is not a revision of the old product (81184-003-03) at all.